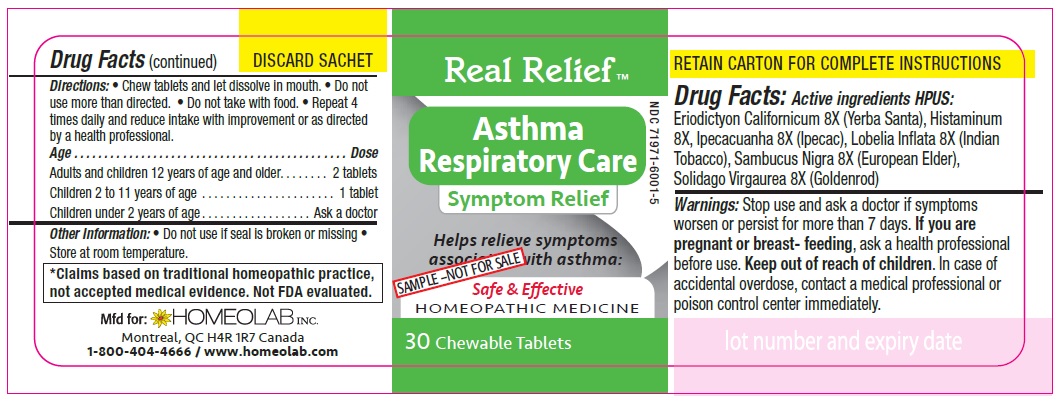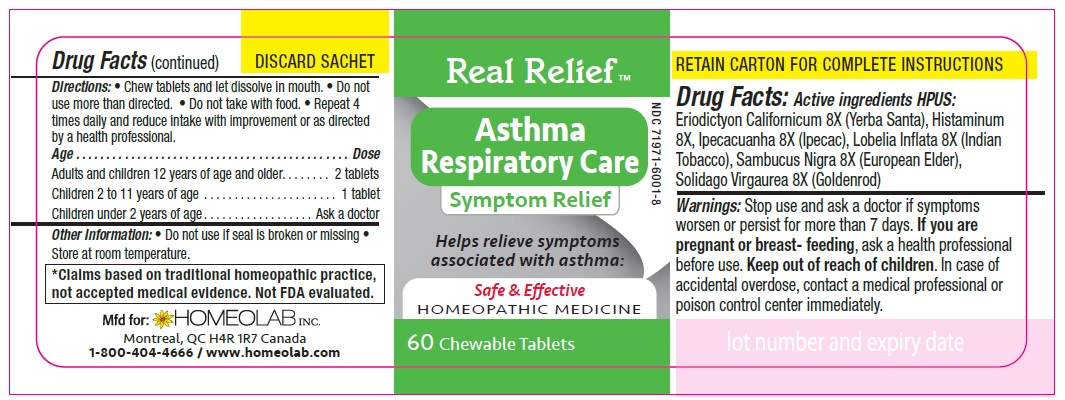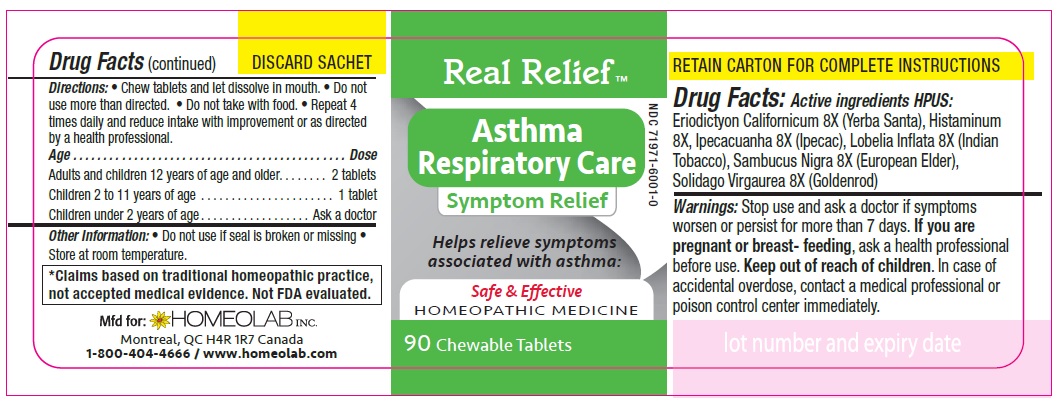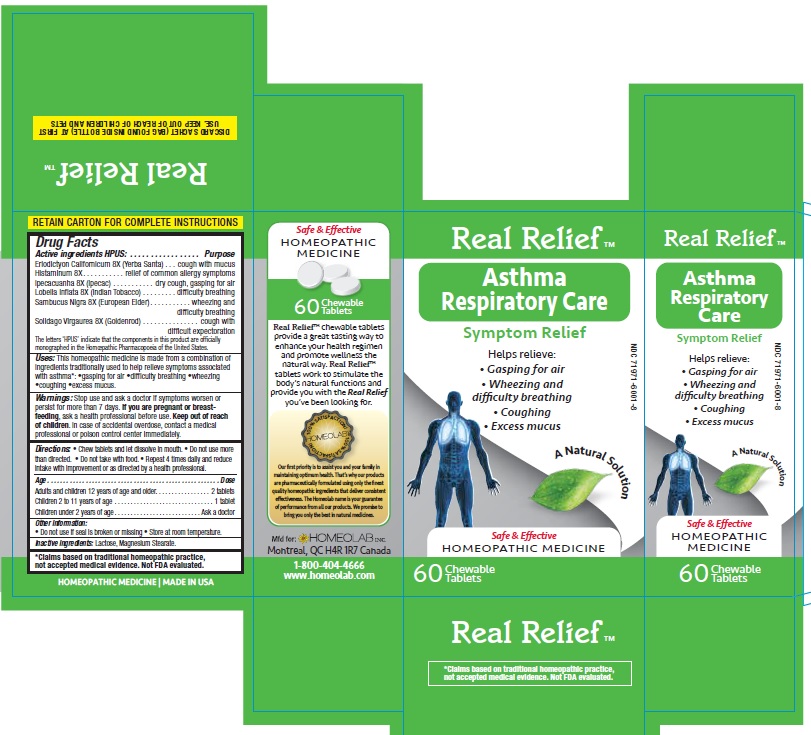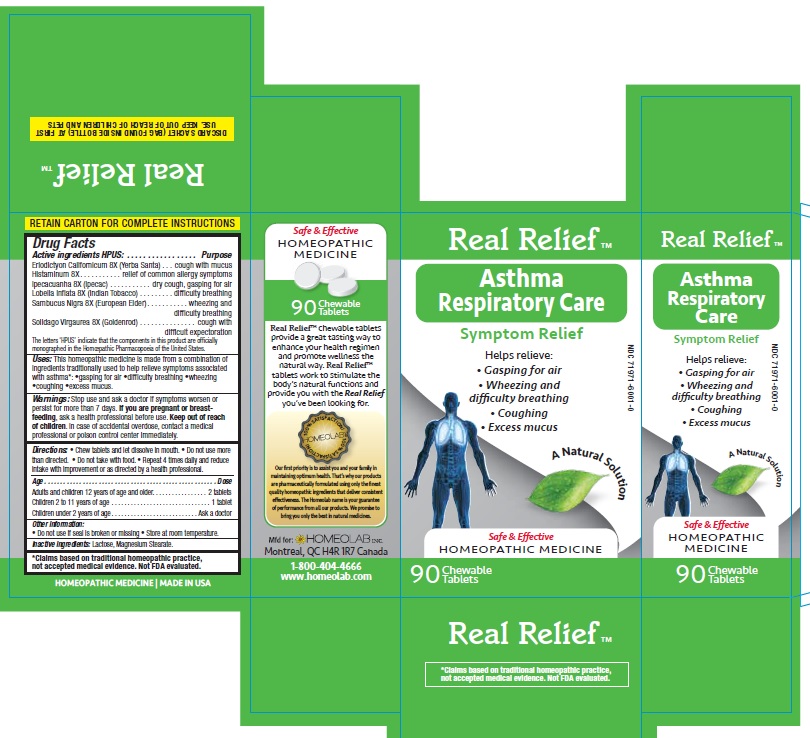 DRUG LABEL: Real Relief
NDC: 65808-320 | Form: TABLET
Manufacturer: GMP Laboratories of America, Inc.
Category: homeopathic | Type: HUMAN OTC DRUG LABEL
Date: 20201229

ACTIVE INGREDIENTS: ERIODICTYON CALIFORNICUM LEAF 8 [hp_X]/1 1; HISTAMINE DIHYDROCHLORIDE 8 [hp_X]/1 1; IPECAC 8 [hp_X]/1 1; LOBELIA INFLATA 8 [hp_X]/1 1; SAMBUCUS NIGRA FLOWERING TOP 8 [hp_X]/1 1; SOLIDAGO VIRGAUREA FLOWERING TOP 8 [hp_X]/1 1
INACTIVE INGREDIENTS: LACTOSE MONOHYDRATE; MAGNESIUM STEARATE

Active Ingredients HPUS:

Eriodictyon californicum (Yerba santa) 8 [hp_X]

Histaminum 8 [hp_X]

Ipecacuanha (Ipecac) 8 [hp_X]

Lobelia inflata (Indian tobacco) 8 [hp_X]

Sambucus nigra (European elder) 8 [hp_X]

Solidago virgaurea (Goldenrod) 8 [hp_X]

Purpose

Homeopathic remedy helps relieve symptoms of asthma:

- gasping for air
- difficulty breathing
- wheezing
- coughing
- excess mucus

The letters 'HPUS' indicate that the components in this product are officially monographed in the Homoeopathic Pharmacopoeia of the United States.
*Claims based on traditional homeopathic practice, not accepted medical evidence. Not FDA evaluated.

Uses

This homeopathic medicine is made from a combination of ingredients traditionally used to help relieve symptoms associated with asthma:

- gasping for air
- difficulty breathing
- wheezing
- coughing
- excess mucus

Warnings

Stop use and ask a doctor if symptoms worsen or last for more than 7 days.

If you are pregnant or breastfeeding, ask a health professional before use.

Keep out of reach of children.

In case of accidental overdose, contact a medical professional or poison control center immediately.

Directions

Chew tablets and let dissolve in mouth.

Do not use more than directed.

Do not take with food.

Repeat 4 times daily and reduce intake with improvement or as directed by a health professional

Age…………………………………………………………........ Dose

Adults and Children 12 years of age and older………...... 2 tablets

Children 2 to 11 years of age…...……………………............ 1 tablet

Children under 2 years of age……………………................. Ask a doctor

Other information

- Store at room temperature.
- Do not use if seal is broken or missing.

Inactive ingredients

Lactose, Magnesium Stearate.